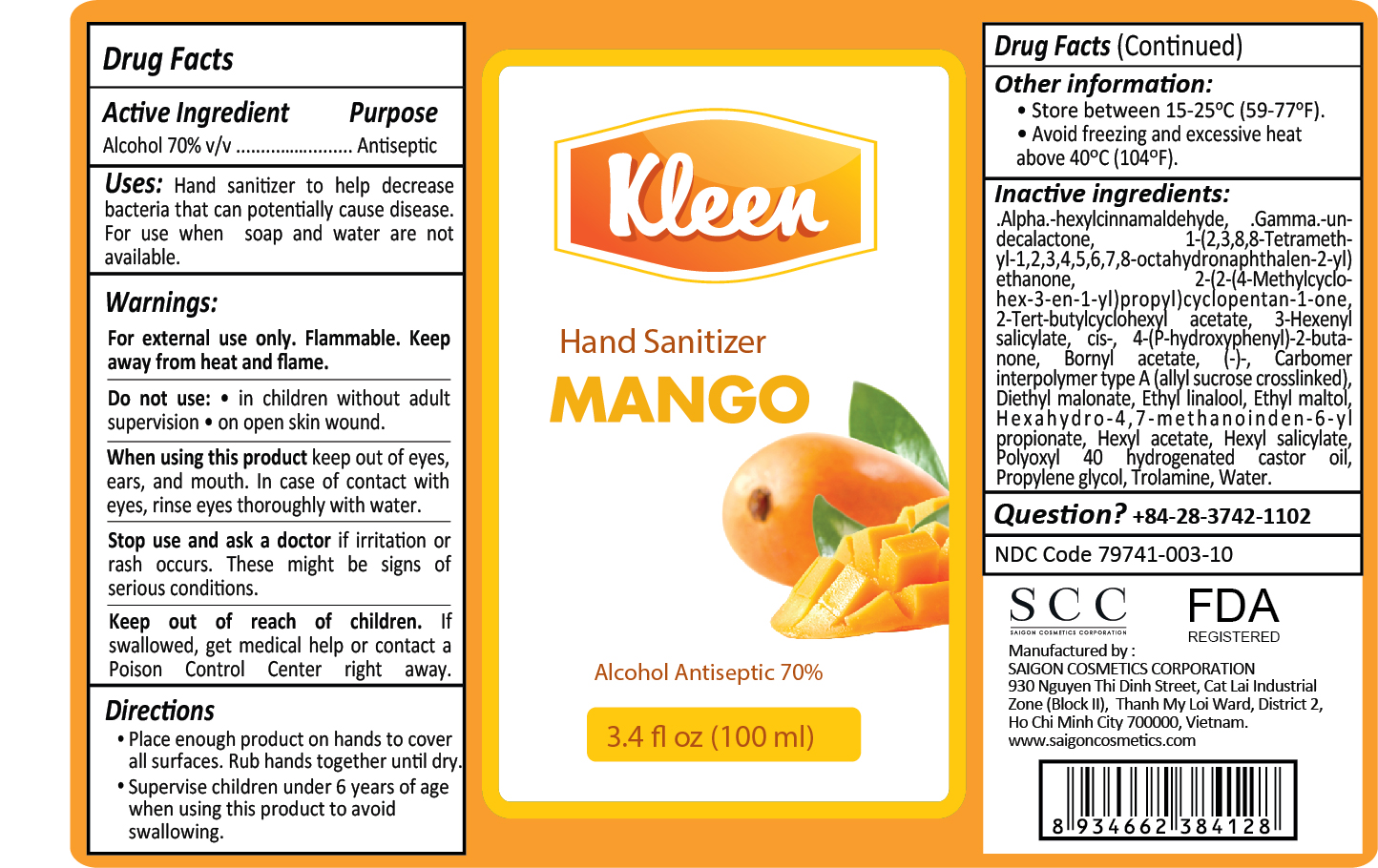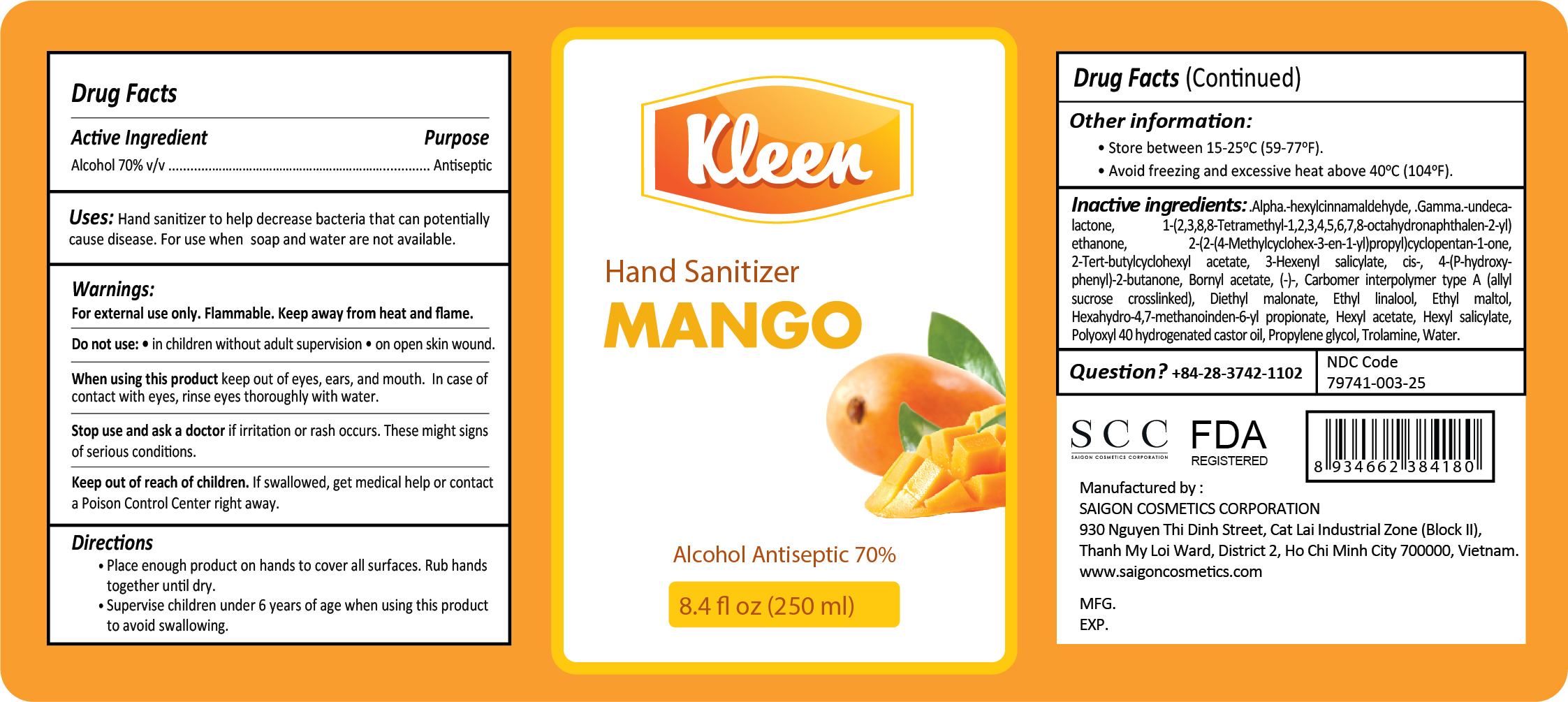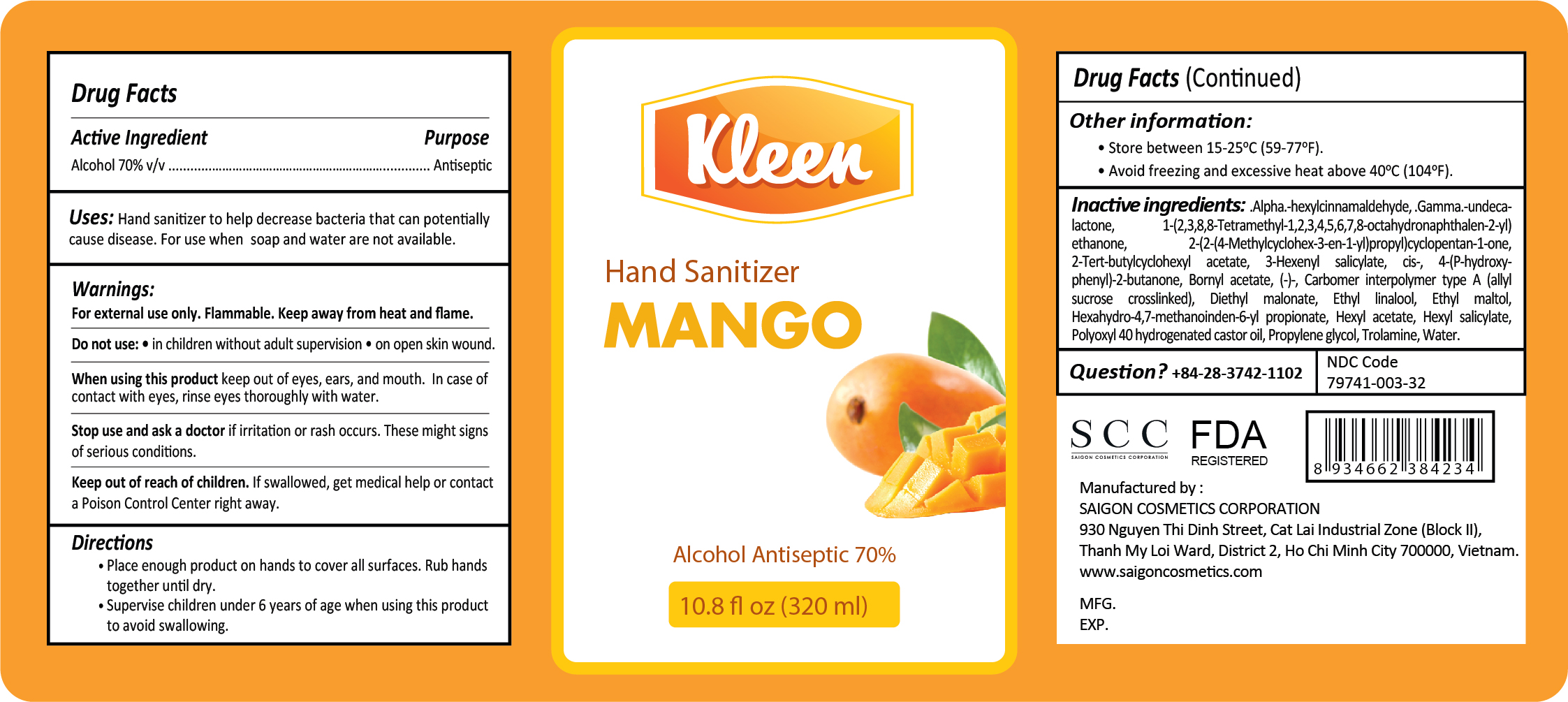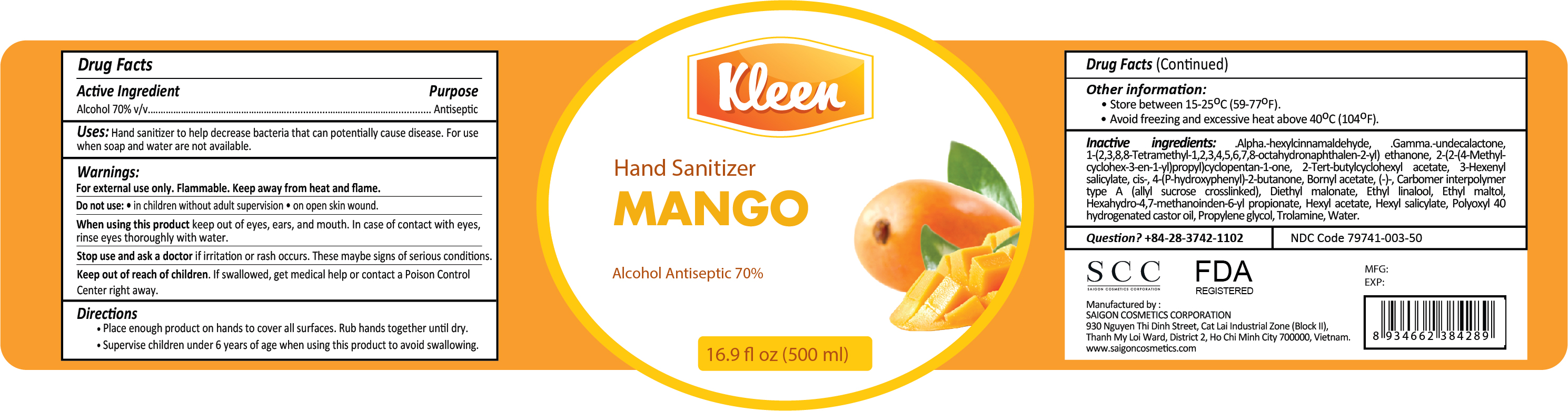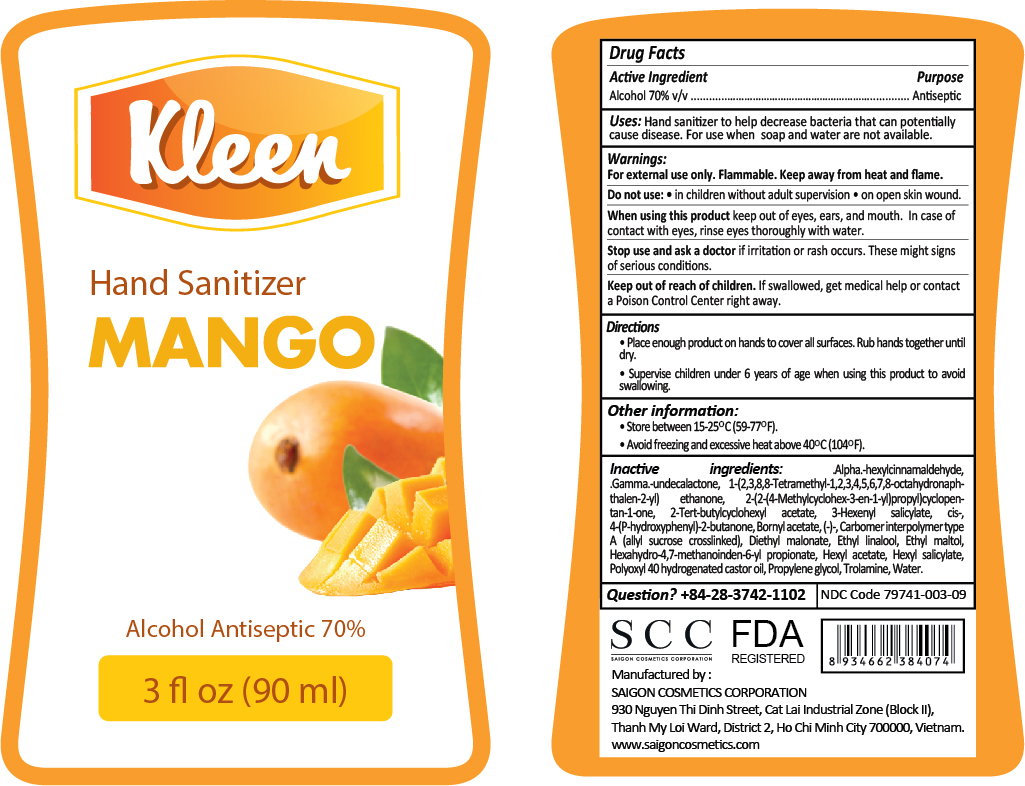 DRUG LABEL: KLEEN HAND SANITIZER MANGO
NDC: 79741-003 | Form: GEL
Manufacturer: SAIGON COSMETICS CORPORATION
Category: otc | Type: HUMAN OTC DRUG LABEL
Date: 20200821

ACTIVE INGREDIENTS: ALCOHOL 70 mL/100 mL
INACTIVE INGREDIENTS: DIETHYL MALONATE; BORNYL ACETATE, (-)-; HEXYL ACETATE; 2-TERT-BUTYLCYCLOHEXYL ACETATE; ETHYL LINALOOL; ETHYL MALTOL; HEXAHYDRO-4,7-METHANOINDEN-6-YL PROPIONATE; 4-(P-HYDROXYPHENYL)-2-BUTANONE; .ALPHA.-HEXYLCINNAMALDEHYDE; 2-(2-(4-METHYLCYCLOHEX-3-EN-1-YL)PROPYL)CYCLOPENTAN-1-ONE; PROPYLENE GLYCOL; CARBOMER INTERPOLYMER TYPE A (ALLYL SUCROSE CROSSLINKED); POLYOXYL 40 HYDROGENATED CASTOR OIL; HEXYL SALICYLATE; 1-(2,3,8,8-TETRAMETHYL-1,2,3,4,5,6,7,8-OCTAHYDRONAPHTHALEN-2-YL)ETHANONE; TROLAMINE; .GAMMA.-UNDECALACTONE; WATER; 3-HEXENYL SALICYLATE, CIS-

ACTIVE INGREDIENT

Alcohol 70% v/v purpose: antiseptic

PURPOSE

Antiseptic, hand sanitizer

INDICATIONS AND USAGE

Hand sanitizer to help decrease bacteria that can potentially cause disease. For use when soap and water are not available.

WARNINGS

For external use only. Flammable. Keep away from heat and flame.

Do not use

- In children without aldult supervision
- On open skin wound

When using this product keep out of eyes, ears, and mouth. In case of contact with eyes, rinse eyes thoroughly with water.

Stop use and ask a doctor if irritation or rash occurs. These may be signs of serious conditions.

Keep out of reach of children. If swallowed, get medical help or contact a poison control center right away.

Directions:

· place enough product on hands to cover all surfaces. Rub hands together until dry.

· supervise children under 6 years of age when using this product to avoid swallowing.

Other information:

- Store between 15-25oC(59-77oF)
- Avoid freezing and excessive heat above 40oC (104oF)

QUESTIONS

+84-28-3742-1102

INACTIVE INGREDIENT

.Alpha.-hexylcinnamaldehyde, .Gamma.-undecalactone, 1-(2,3,8,8-Tetramethyl-1,2,3,4,5,6,7,8-octahydronaphthalen-2-Yl)ethanone, 2-(2-(4-Methylcyclohex-3-en-1-Yl)propyl)cyclopentan-1-one, 2-Tert-butylcyclohexyl acetate, 3-Hexenyl salicylate, cis-, 4-(P-hydroxyphenyl)-2-butanone, Bornyl acetate, (-)-, Carbomer interpolymer type A (allyl sucrose crosslinked), Diethyl malonate, Ethyl linalool, Ethyl maltol, Hexahydro-4,7-methanoinden-6-yl propionate, Hexyl acetate, Hexyl salicylate, Polyoxyl 40 hydrogenated castor oil, Propylene glycol, Trolamine, Water